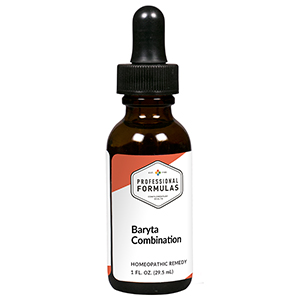 DRUG LABEL: Baryta Combination
NDC: 63083-9209 | Form: LIQUID
Manufacturer: Professional Complementary Health Formulas
Category: homeopathic | Type: HUMAN OTC DRUG LABEL
Date: 20190815

ACTIVE INGREDIENTS: ARNICA MONTANA WHOLE 4 [hp_X]/29.5 mL; DATURA STRAMONIUM 4 [hp_X]/29.5 mL; SEMECARPUS ANACARDIUM JUICE 6 [hp_X]/29.5 mL; BARIUM CHLORIDE DIHYDRATE 6 [hp_X]/29.5 mL; CAUSTICUM 6 [hp_X]/29.5 mL; STRYCHNOS IGNATII SEED 6 [hp_X]/29.5 mL; CALCIUM IODIDE 8 [hp_X]/29.5 mL; POTASSIUM PHOSPHATE, UNSPECIFIED FORM 8 [hp_X]/29.5 mL; ACONITUM NAPELLUS WHOLE 12 [hp_X]/29.5 mL; BARIUM CARBONATE 12 [hp_X]/29.5 mL
INACTIVE INGREDIENTS: ALCOHOL; WATER

R209

ACTIVE INGREDIENTS

Arnica montana 4X
Stramonium 4X
Anacardium orientale 6X
Baryta muriatica 6X
Causticum 6X
Ignatia amara 6X
Calcarea iodata 8X
Kali phosphoricum 8X
Aconitum napellus 12X
Baryta carbonica 12X

QUESTIONS

Professional Formulas

PO Box 2034 Lake Oswego, OR 97035

INDICATIONS

For the temporary relief of minor sore throat, cough, sneezing, runny nose, or nasal congestion.*

PURPOSE

*Claims based on traditional homeopathic practice, not accepted medical evidence. Not FDA evaluated.

WARNINGS

If symptoms do not improve or are accompanied by a fever, consult a doctor. Keep out of the reach of children. In case of overdose, get medical help or contact a poison control center right away. If pregnant or breastfeeding, ask a healthcare professional before use.

Keep out of the reach of children.

PREGNANCY OR BREAST FEEDING

If pregnant or breastfeeding, ask a healthcare professional before use.

DIRECTIONS

Place drops under tongue 30 minutes before/after meals. Adults and children 12 years and over: Take 10 drops up to 3 times per day. Consult a physician for use in children under 12 years of age.

OTHER INFORMATION

Tamper resistant. If seal is broken, do not use. After opening, close container tightly and store at room temperature away from heat.

INACTIVE INGREDIENTS

40% ethanol, purified water.

LABEL

Est 1985

Professional Formulas

Complementary Health

Baryta Combination

Homeopathic Remedy

1 FL. OZ. (29.5 mL)